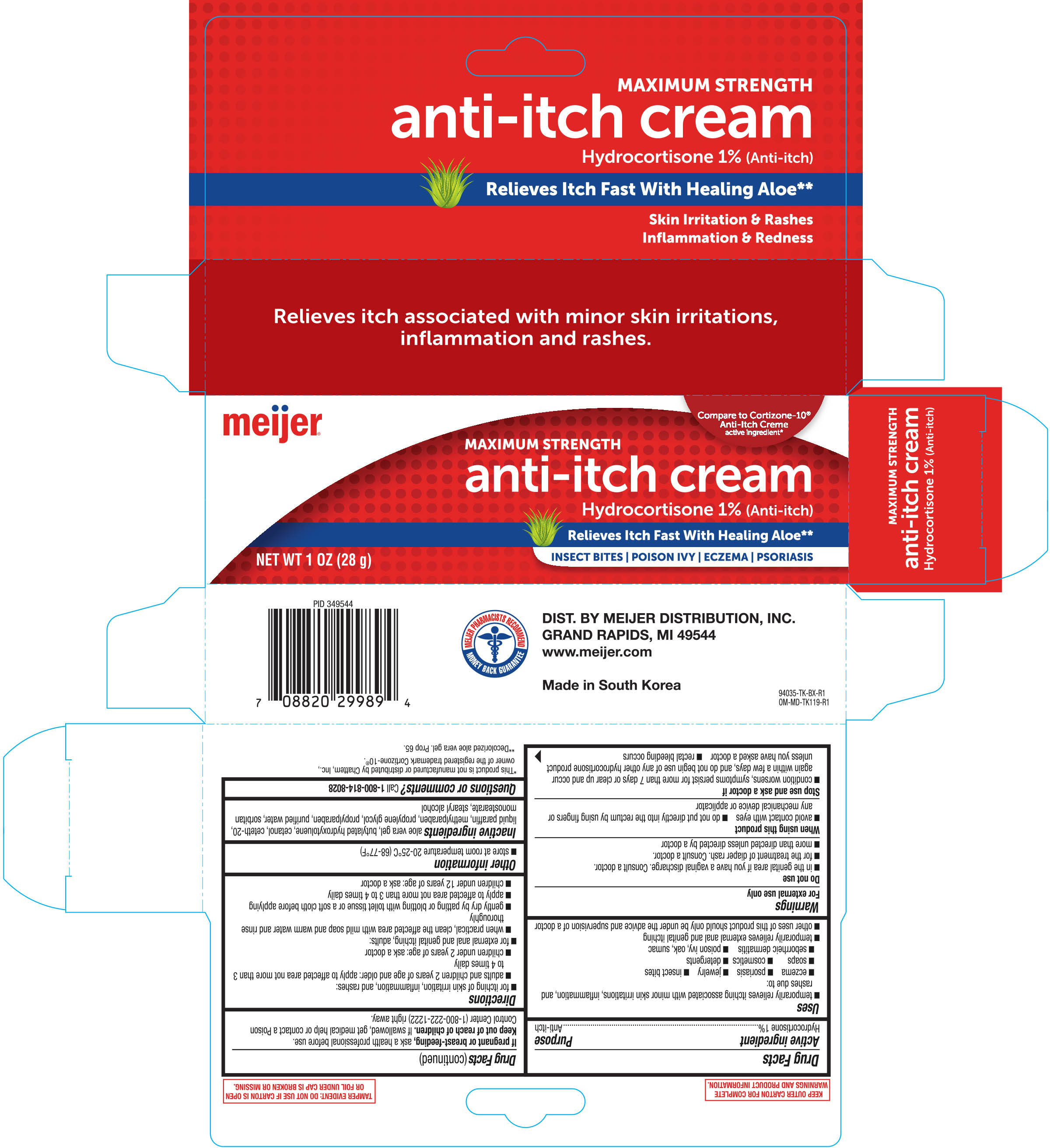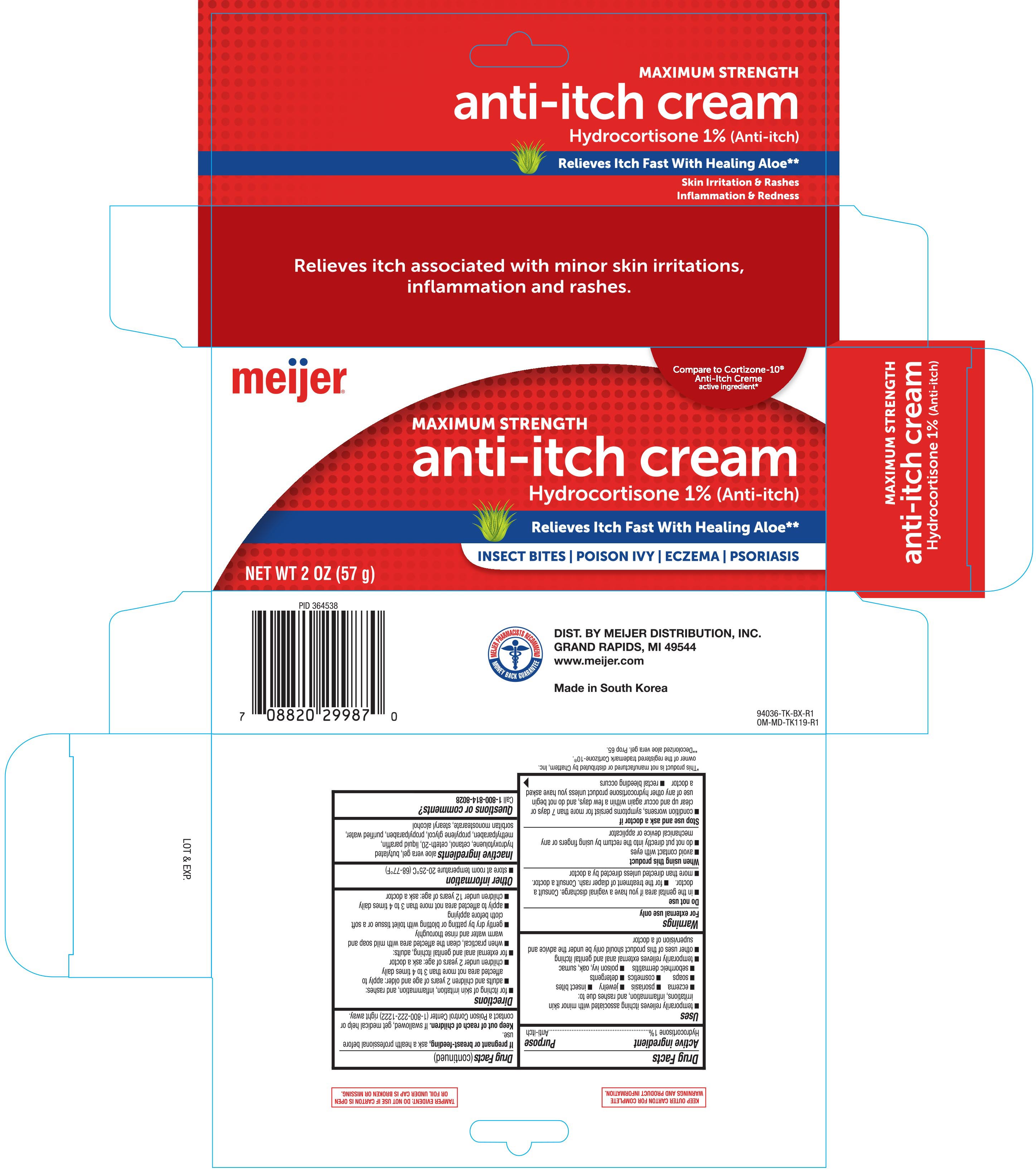 DRUG LABEL: anti-itch
NDC: 41250-945 | Form: OINTMENT
Manufacturer: Meijer, Inc.
Category: otc | Type: HUMAN OTC DRUG LABEL
Date: 20181218

ACTIVE INGREDIENTS: HYDROCORTISONE 10 mg/1 g
INACTIVE INGREDIENTS: BUTYLATED HYDROXYTOLUENE; PROPYLPARABEN; ALOE VERA LEAF; CETYL ALCOHOL; METHYLPARABEN; PROPYLENE GLYCOL; SORBITAN MONOSTEARATE; STEARYL ALCOHOL; MINERAL OIL; CETETH-20; WATER

Meijer Anti-Itch Cream 1oz (94035, 2018)
Meijer Anti-Itch Cream 2oz (94036, 2018)

Active ingredient Purpose

Hydrocortisone 1%................Anti-itch

Uses

- temporarily relieves itching associated with minor skin irritations, inflammation, and rashes due to:
- eczema
- psoriasis
- jewelry
- insect bites
- soaps
- cosmetics
- detergents
- seborrheic dermatitis
- poison ivy, oak, sumac
- temporarily relieves external anal and genital itching
- other uses of this product should only be under the advice and supervision of a doctor

WARNINGS

For external use only

Do not use

- in the genital area if you have a vaginal discharge. Consult a doctor.
- for the treatment of diaper rash. Consult a doctor.
- more than directed unless directed by a doctor

When using this product

- avoid contact with eyes
- do not put directly into the rectum by using fingers or any mechanical device or applicator

Stop use and ask a doctor if

- condition worsens, symptoms persist for more than 7 days or clear up and occur again within a few days, and do not begin use of any other hydrocortisone product unless you have asked a doctor
- rectal bleeding occurs

PREGNANCY OR BREAST FEEDING

If pregnant or breast-fedding, aska health professional before use.

Keep out of reach of children. If swallowed, get medical help or contact a Poison Control Center (1-800-222-1222) right away.

INDICATIONS AND USAGE

- for itching of skin irritation, inflammation, and rashes:
- adults and children 2 years of age and older: apply to affected area not more than 3 to 4 times daily
- children under 2 years of age: ask a doctor
- for external anal and genital itching, adults:
- when practical, clean the affected area with mild soap and warm water and rinse thoroughly
- gently dry by patting or blotting with toilet tissue or a soft cloth before applying
- apply to affected area not more than 3 to 4 times daily
- children under 12 years of age: ask a doctor

STORAGE AND HANDLING

- store at room temperature 20-25°C (68-77°F)

INACTIVE INGREDIENT

aloe vera gel, butylated hydroxytoluene, cetanol, ceteth-20, liquid paraffin, methylparaben, propylene glycol, propylparaben, purified water, sorbitan monostearate, stearyl alcohol

Questions or comments?

Call 1-800-814-8028

DOSAGE AND ADMINISTRATION

DIST. BY MEIJER DISTRIBUTION, INC.

GRAND RAPIDS, MI 49544

www.meijer,com

Made in South Korea